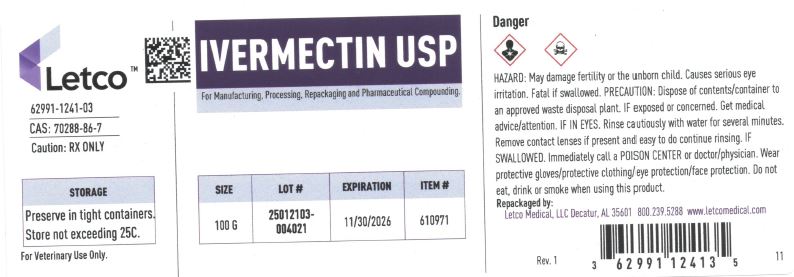 DRUG LABEL: Ivermectin
NDC: 62991-1241 | Form: POWDER
Manufacturer: LETCO MEDICAL, LLC
Category: other | Type: BULK INGREDIENT - ANIMAL DRUG
Date: 20250627

ACTIVE INGREDIENTS: IVERMECTIN 1 g/1 g

Ivermectin

PACKAGE LABEL

Ivermectin USP 100g